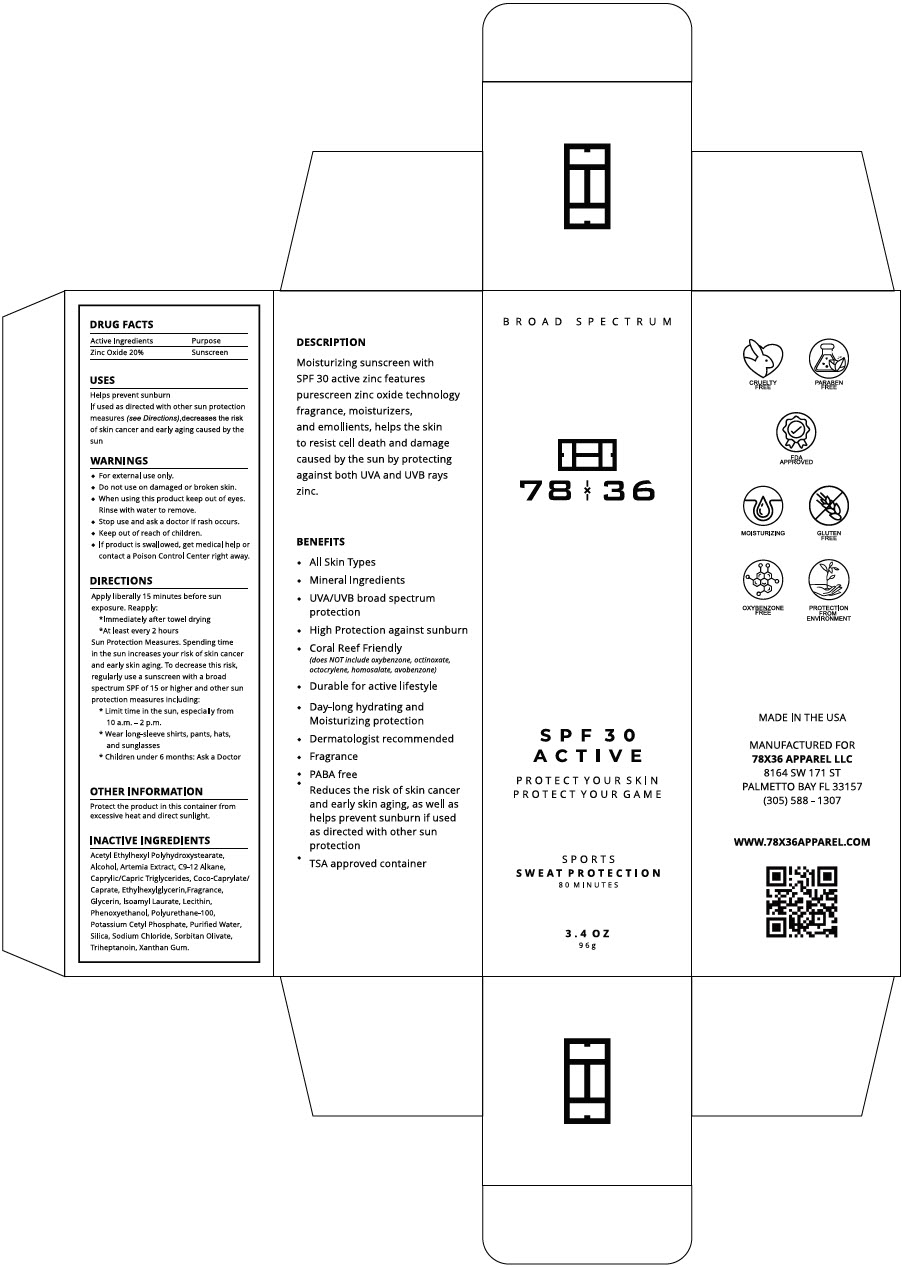 DRUG LABEL: 78 x 36 SPF 30 Active
NDC: 58466-109 | Form: CREAM
Manufacturer: Dermazone LLC
Category: otc | Type: HUMAN OTC DRUG LABEL
Date: 20250725

ACTIVE INGREDIENTS: ZINC OXIDE 0.2 g/1 g
INACTIVE INGREDIENTS: ALCOHOL; C9-12 ALKANE; MEDIUM-CHAIN TRIGLYCERIDES; COCOYL CAPRYLOCAPRATE; ETHYLHEXYLGLYCERIN; GLYCERIN; PHENOXYETHANOL; POTASSIUM CETYL PHOSPHATE; WATER; SILICON DIOXIDE; SODIUM CHLORIDE; SORBITAN OLIVATE; TRIHEPTANOIN; XANTHAN GUM

78 x 36 SPF 30 Active

DRUG FACTS

Active Ingredients

Zinc Oxide 20%

Purpose

Sunscreen

USES

Helps prevent sunburn

lf used as directed with other sun protection measures (see Directions),decreases the risk of skin cancer and early aging caused by the sun

WARNINGS

- For external use only.

- Do not use on damaged or broken skin.

- When using this product keep out of eyes. Rinse with water to remove.

- Stop use and ask a doctor if rash occurs.

- Keep out of reach of children.
- If product is swallowed, get medical help or contact a Poison Control Center right away.

DIRECTIONS

Apply liberally 15 minutes before sun exposure. Reapply:

- Immediately after towel drying
- At least every 2 hours

Sun Protection Measures

Spending time in the sun increases your risk of skin cancer and early skin aging. To decrease this risk, regularly use a sunscreen with a broad spectrum SPF of 15 or higher and other sun protection measures including:

- Limit time in the sun, especially from 10 a.m. - 2 p.m.
- Wear long-sleeve shirts, pants, hats, and sunglasses
- Children under 6 months: Ask a Doctor

OTHER INFORMATION

Protect the product in this container from excessive heat and direct sunlight.

INACTIVE INGREDIENTS

Acetyl Ethylhexyl Polyhydroxystearate, Alcohol, Artemia Extract, C9-12 Alkane, Caprylic/Capric Triglycerides, Coco-Caprylate/Caprate, Ethylhexylglycerin,Fragrance, Glycerin, Isoamyl Laurate, Lecithin, Phenoxyethanol, Polyurethane-100, Potassium Cetyl Phosphate, Purified Water, Silica, Sodium Chloride, Sorbitan Olivate, Triheptanoin, Xanthan Gum.

PRINCIPAL DISPLAY PANEL - 96 g Tube Carton

BROAD SPECTRUM

78 x 36

SPF 30
ACTIVE

PROTECT YOUR SKIN
PROTECT YOUR GAME

SPORTS
SWEAT PROTECTION
80 MINUTES

3.4 OZ
96g